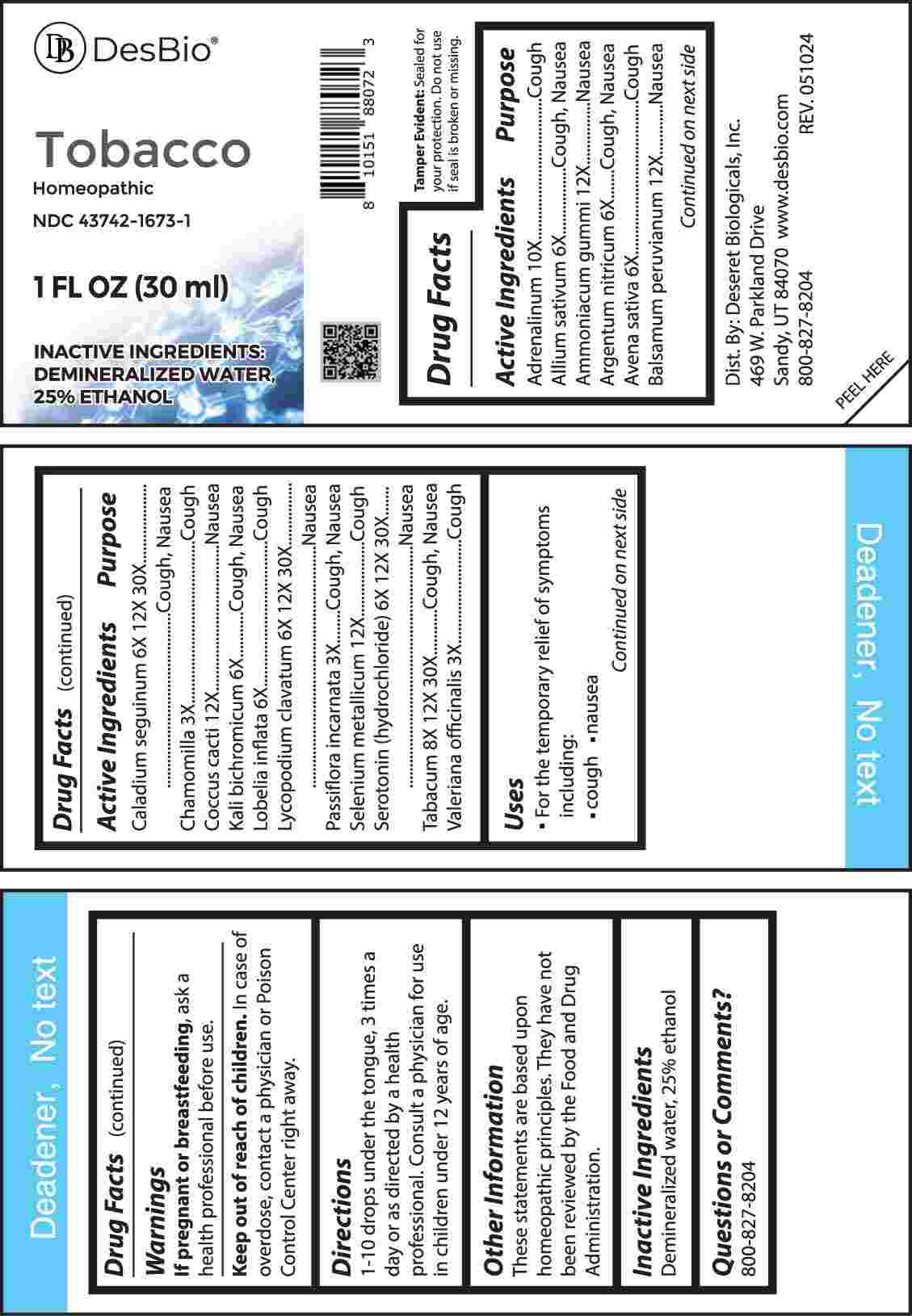 DRUG LABEL: Tobacco
NDC: 43742-1673 | Form: LIQUID
Manufacturer: Deseret Biologicals, Inc.
Category: homeopathic | Type: HUMAN OTC DRUG LABEL
Date: 20240923

ACTIVE INGREDIENTS: MATRICARIA CHAMOMILLA WHOLE 3 [hp_X]/1 mL; PASSIFLORA INCARNATA FLOWERING TOP 3 [hp_X]/1 mL; VALERIAN 3 [hp_X]/1 mL; GARLIC 6 [hp_X]/1 mL; SILVER NITRATE 6 [hp_X]/1 mL; AVENA SATIVA FLOWERING TOP 6 [hp_X]/1 mL; DIEFFENBACHIA SEGUINE WHOLE 6 [hp_X]/1 mL; POTASSIUM DICHROMATE 6 [hp_X]/1 mL; LOBELIA INFLATA WHOLE 6 [hp_X]/1 mL; LYCOPODIUM CLAVATUM SPORE 6 [hp_X]/1 mL; SEROTONIN HYDROCHLORIDE 6 [hp_X]/1 mL; TOBACCO LEAF 8 [hp_X]/1 mL; EPINEPHRINE 10 [hp_X]/1 mL; FERULA AMMONIACUM RESIN 12 [hp_X]/1 mL; BALSAM PERU 12 [hp_X]/1 mL; PROTORTONIA CACTI 12 [hp_X]/1 mL; SELENIUM 12 [hp_X]/1 mL
INACTIVE INGREDIENTS: WATER; ALCOHOL

DRUG FACTS:

ACTIVE INGREDIENTS:

Adrenalinum 10X, Allium Sativum 6X, Ammoniacum Gummi 12X, Argentum Nitricum 6X, Avena Sativa 6X, Balsamum Peruvianum 12X, Caladium Seguinum 6X, 12X, 30X, Chamomilla 3X, Coccus Cacti 12X, Kali Bichromicum 6X, Lobelia Inflata 6X, Lycopodium Clavatum 6X, 12X, 30X, Passiflora Incarnata 3X, Selenium Metallicum 12X, Serotonin (Hydrochloride) 6X, 12X, 30X, Tabacum 8X, 12X, 30X, Valeriana Officinalis 3X.

PURPOSE:

Adrenalinum - Cough, Allium Sativum – Cough, Nausea, Ammoniacum Gummi - Nausea, Argentum Nitricum – Cough, Nausea, Avena Sativa - Cough, Balsamum Peruvianum - Nausea, Caladium Seguinum – Cough, Nausea, Chamomilla - Cough, Coccus Cacti - Nausea, Kali Bichromicum – Cough, Nausea, Lobelia Inflata - Cough, Lycopodium Clavatum - Nausea, Passiflora Incarnata – Cough, Nausea, Selenium Metallicum - Cough, Serotonin (Hydrochloride) - Nausea, Tabacum – Cough, Nausea, Valeriana Officinalis - Cough

USES:

• For the temporary relief of symptoms including:

• cough • nausea

These statements are based upon homeopathic principles. They have not been reviewed by the Food and Drug Administration.

WARNINGS:

If pregnant or breast-feeding, ask a health professional before use.

Keep out of reach of children. In case of overdose, contact a physician or Poison Control Center right away.

Tamper Evident: Sealed for your protection. Do not use if seal is broken or missing.

KEEP OUT OF REACH OF CHILDREN:

In case of overdose, contact a physician or Poison Control Center right away.

DIRECTIONS:

1-10 drops under the tongue, 3 times a day or as directed by a health professional. Consult a physician for use in children under 12 years of age.

INACTIVE INGREDIENTS:

Demineralized water, 25% ethanol

QUESTIONS:

Dist. By: Deseret Biologicals, Inc.

469 W. Parkland Drive

Sandy, UT 84070

www.desbio.com

800-827-8204

PACKAGE LABEL DISPLAY:

DesBio

Tobacco

Homeopathic

NDC 43742-1673-1

1 FL OZ (30 ml)